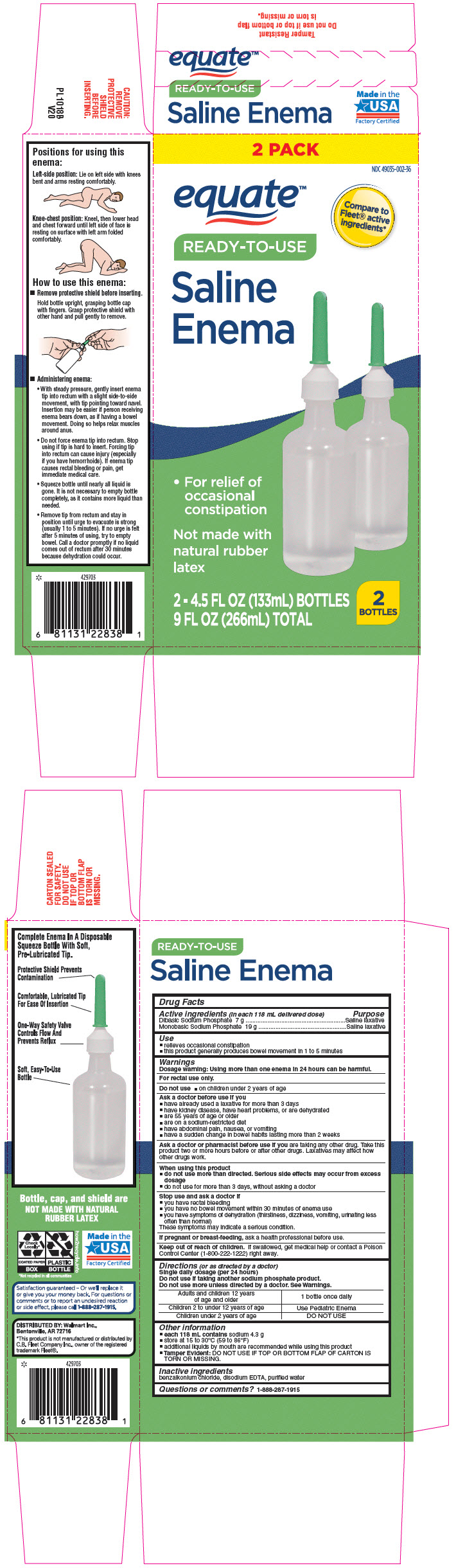 DRUG LABEL: Equate Ready-to-Use Enema
NDC: 49035-002 | Form: ENEMA
Manufacturer: WalMart
Category: otc | Type: HUMAN OTC DRUG LABEL
Date: 20260129

ACTIVE INGREDIENTS: SODIUM PHOSPHATE, DIBASIC, UNSPECIFIED FORM 7 g/118 mL; SODIUM PHOSPHATE, MONOBASIC, UNSPECIFIED FORM 19 g/118 mL
INACTIVE INGREDIENTS: BENZALKONIUM CHLORIDE; EDETATE DISODIUM; WATER

Equate™ Ready-to-Use Enema
Laxative

Drug Facts

ACTIVE INGREDIENT

PURPOSE

Active ingredients (in each 118 mL delivered dose) | Purpose
Dibasic Sodium Phosphate 7 g | Saline laxative
Monobasic Sodium Phosphate 19 g | Saline laxative

Use

- relieves occasional constipation
- this product generally produces bowel movement in 1 to 5 minutes

Warnings

Dosage warning

Using more than one enema in 24 hours can be harmful.

For rectal use only.

Do not use

- on children under 2 years of age

Ask a doctor before use if you

- have already used a laxative for more than 3 days
- have kidney disease, have heart problems, or are dehydrated
- are 55 years of age or older
- are on a sodium-restricted diet
- have abdominal pain, nausea, or vomiting
- have a sudden change in bowel habits lasting more than 2 weeks

Ask a doctor or pharmacist before use if you are taking any other drug. Take this product two or more hours before or after other drugs. Laxatives may affect how other drugs work.

When using this product

- do not use more than directed. Serious side effects may occur from excess dosage
- do not use for more than 3 days, without asking a doctor

Stop use and ask a doctor if

- you have rectal bleeding
- you have no bowel movement within 30 minutes of enema use
- you have symptoms of dehydration (thirstiness, dizziness, vomiting, urinating less often than normal)

These symptoms may indicate a serious condition.

PREGNANCY OR BREAST FEEDING

If pregnant or breast-feeding, ask a health professional before use.

Keep out of reach of children. If swallowed, get medical help or contact a Poison Control Center (1-800-222-1222) right away.

Directions (or as directed by a doctor)

Single daily dosage (per 24 hours)

Do not use if taking another sodium phosphate product.

Do not use more unless directed by a doctor. See Warnings.

Adults and children 12 years of age and older | 1 bottle once daily
Children 2 to under 12 years of age | Use Pediatric Enema
Children under 2 years of age | DO NOT USE

Other information

- each 118 mL contains sodium 4.3 g
- store at 15 to 30°C (59 to 86°F)
- additional liquids by mouth are recommended while using this product
- Tamper Evident: DO NOT USE IF TOP OR BOTTOM FLAP OF CARTON IS TORN OR MISSING.

Inactive ingredients

benzalkonium chloride, disodium EDTA, purified water

Questions or comments?

1-888-287-1915

DISTRIBUTED BY: Wal-Mart, Inc.,
Bentonville, AR 72716

PRINCIPAL DISPLAY PANEL - 2 Bottle Carton

2 PACK

NDC 49035-002-36

equate™

Compare to
Fleet® active
ingredients*

READY-TO-USE

Saline
Enema

- For relief of
  occasional
  constipation

Not made with
natural rubber
latex

2 - 4.5 FL OZ (133mL) BOTTLES
9 FL OZ (266mL) TOTAL

2
BOTTLES